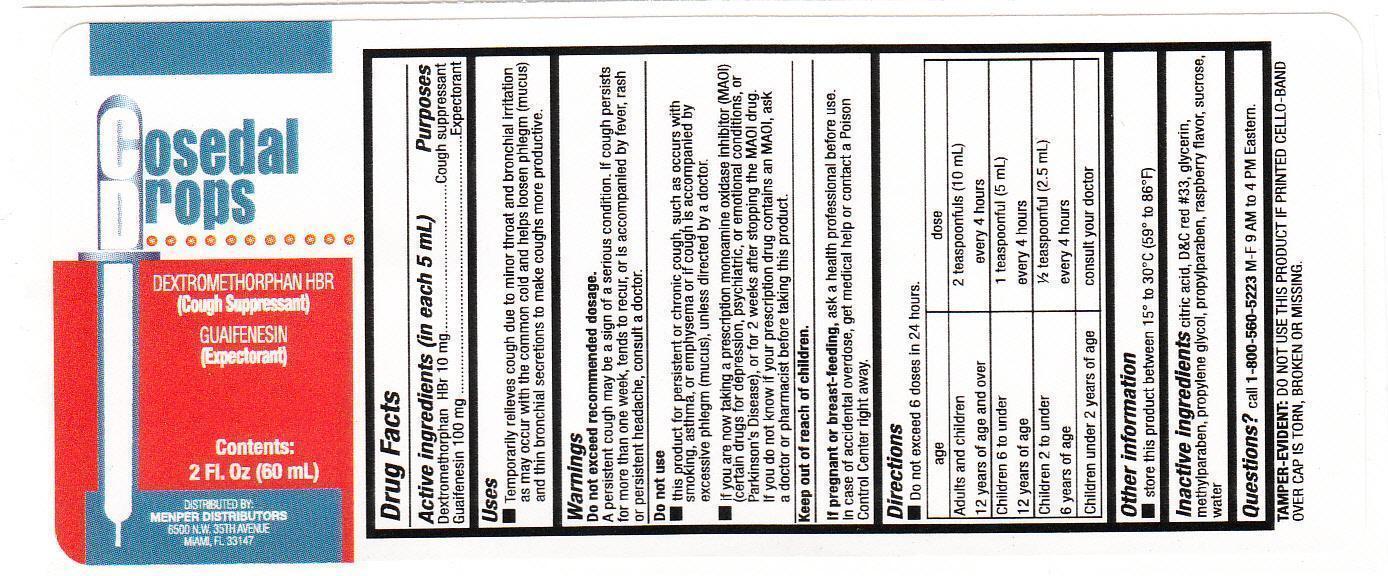 DRUG LABEL: Cosedal Drops
NDC: 53145-059 | Form: LIQUID
Manufacturer: Menper Distributors, Inc.
Category: otc | Type: HUMAN OTC DRUG LABEL
Date: 20250722

ACTIVE INGREDIENTS: DEXTROMETHORPHAN HYDROBROMIDE 10 mg/5 mL; GUAIFENESIN 100 mg/5 mL
INACTIVE INGREDIENTS: ANHYDROUS CITRIC ACID; D&C RED NO. 33; GLYCERIN; METHYLPARABEN; PROPYLENE GLYCOL; PROPYLPARABEN; SUCROSE; WATER

Cosedal Drops

Active ingredients

Dextromethorphan HBR

Guaifenesin

Purpose

Cough Suppressant

Expectorant

Uses

- Temporarily relieves cough due to minor throat and bronchial irritation as may occur with the common cold and help loosen phlegm (mucus) and thin bronchial secretions to make coughs more productive.

Warnings

Do not exceed recommended dosage.

- A persistent cough may be a sign of a serious condition. If cough persists more than one week, tends to reoccur, or is accompanied by fever, rash, or persistent headache, consult a doctor.

Do not use:

- This product for persistent or chronic cough, such as occurs with smoking, asthma, or emphysema or if cough is accompanied by excessive phlegm (mucus), unless directed by a doctor.
- if you are now taking a prescription monoamine oxidase inhibitor (MAOI) (certain drugs for depression, psychiatric or emotional conditions, or Parkinson’s disease), or for 2 weeks after stopping the MAOI drug. If you do not know if your prescription drug contains an MAOI, ask a doctor or pharmacist before taking this product.

Keep out of reach of children.

PREGNANCY OR BREAST FEEDING

If you are pregnant or breast-feeding,ask a health professional before use.

In case of accidental overdose, get medical help or contact a Poison Control Center right away.

Directions

Do not exceed 6 doses in 24 hours.

age | dose
12 years of age and over | 2 teaspoonfuls (10 mL) every 4 hours
Children 6 to under 12 years of age | 1 teaspoonful (5 mL) every 4 hours
Children 2 to under 6 years of age | 1/2 teaspoonful (2.5 mL) every 4 hours
Children under 2 years of age | consult your doctor

Other information

Store this product between 15°-30°C (59°-86°F)

INACTIVE INGREDIENT

Inactive ingredientsCitric acid, D&C red #33, glycerin, methylparaben, propylene glycol, propylparaben, raspberry falvor, sucrose, water

QUESTIONS

Questions?call 1-800-560-5223M-F 9 AM to 4 PM Eastern.